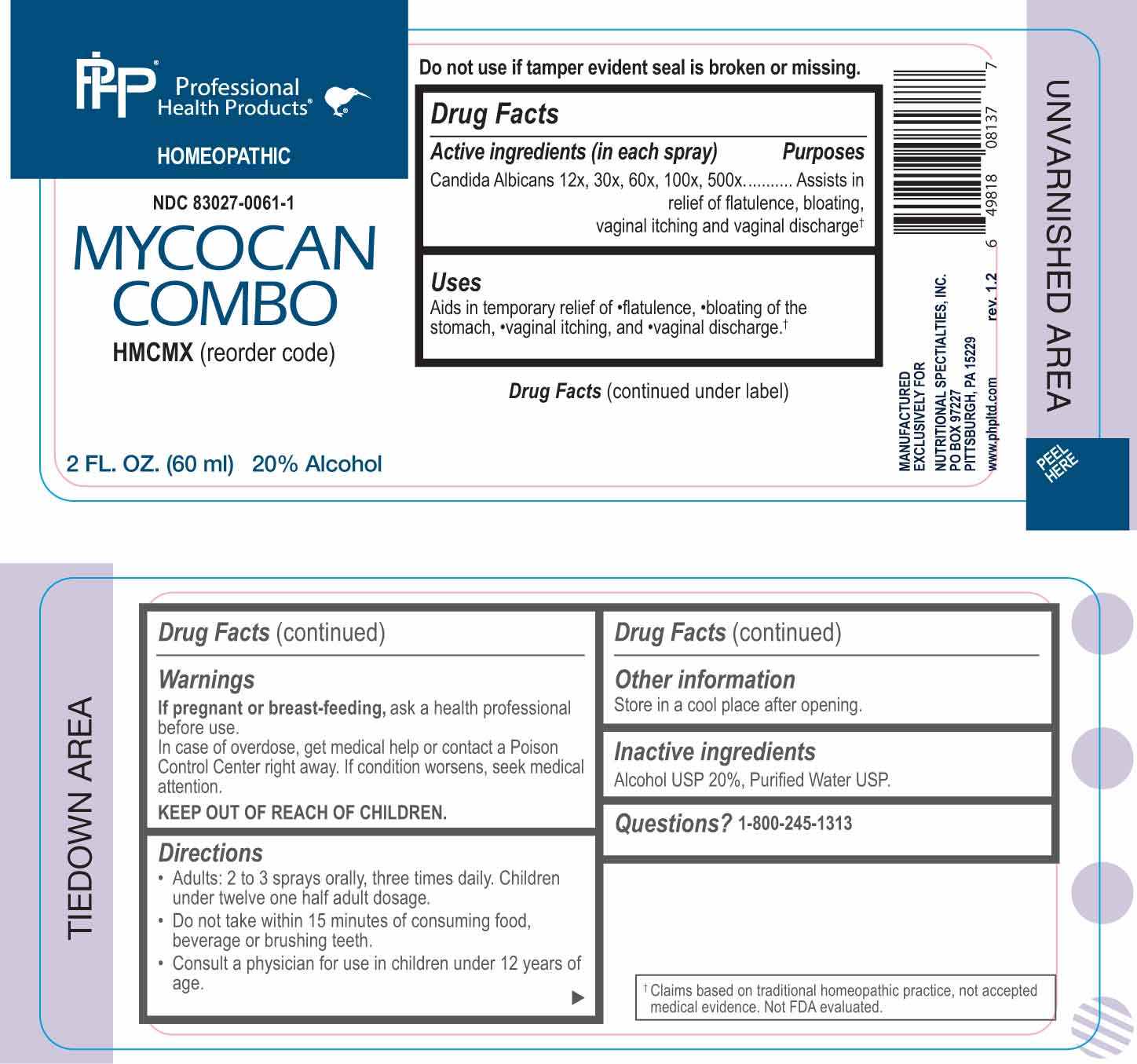 DRUG LABEL: Mycocan Combo
NDC: 83027-0061 | Form: SPRAY
Manufacturer: Nutritional Specialties, Inc.
Category: homeopathic | Type: HUMAN OTC DRUG LABEL
Date: 20250407

ACTIVE INGREDIENTS: CANDIDA ALBICANS 12 [hp_X]/1 mL
INACTIVE INGREDIENTS: WATER; ALCOHOL

DRUG FACTS:

ACTIVE INGREDIENTS:

Candida Albicans 12X, 30X, 60X, 100X, 500X.

PURPOSE:

Candida Albicans - Assists in relief of flatulence, bloating, vaginal itching and vaginal discharge

†Claims based on traditional homeopathic practice, not accepted medical evidence. Not FDA evaluated.

USES:

Aids in temporary relief of flatulence, bloating of the stomach, vaginal itching, and vaginal discharge.†

†Claims based on traditional homeopathic practice, not accepted medical evidence. Not FDA evaluated.

WARNINGS:

If pregnant or breast-feeding, ask a health professional before use.

In case of overdose, get medical help or contact a Poison Control Center right away.

If condition worsens, seek medical attention.

KEEP OUT OF REACH OF CHILDREN

Do not use if tamper evident seal is broken or missing.

Store in a cool place after opening

KEEP OUT OF REACH OF CHILDREN:

In case of overdose, get medical help or contact a Poison Control Center right away.

DIRECTIONS:

• Adults: 2 to 3 sprays orally, three times daily. Children under twelve one half adult dosage.

• Do not take within 15 minutes of consuming food, beverage or brushing teeth.

Consult a physician for use in children under 12 years of age.

INACTIVE INGREDIENTS:

Alcohol USP 20%, Purified Water USP.

QUESTIONS:

MANUFACTURED EXCLUSIVELY FOR

NUTRITIONAL SPECIALTIES, INC.

PO BOX 97227

PITTSBURG, PA 15229

www.phpltd.com

1-800-245-1313

PACKAGE LABEL DISPLAY:

Professional

Health Products

HOMEOPATHIC

NDC 83027-0061-1

MYCOCAN COMBO

2 FL. OZ (60 ml)